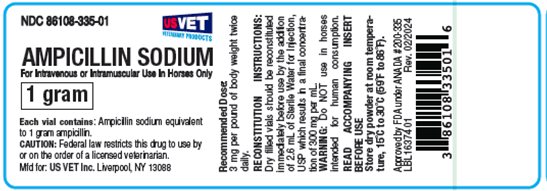 DRUG LABEL: Ampicillin Sodium
NDC: 86108-335 | Form: INJECTION, POWDER, FOR SOLUTION
Manufacturer: US Vet Inc
Category: animal | Type: PRESCRIPTION ANIMAL DRUG LABEL
Date: 20240306

ACTIVE INGREDIENTS: AMPICILLIN SODIUM 1 g/1 1

Ampicillin Sodium
For Intravenous or Intramuscular Use in Horses Only

DESCRIPTION

Ampicillin sodium is a semisynthetic penicillin with a broad spectrum of activity. Ampicillin is derived from the penicillin nucleus, 6-aminopenicillanic acid (6 APA). Chemically it is D(-)α-aminobenzyl penicillin sodium salt.

ACTION

Ampicillin sodium provides bactericidal activity against a wide range of common Gram-positive and Gram-negative pathogens. Ampicillin’s activity occurs during the stage of active multiplication of the pathogen and acts through inhibition of biosynthesis of cell wall mucopeptide. In vivo studies have demonstrated the susceptibility of many strains of the following Gram-positive bacteria: Staphylococcus spp. and Streptococcus spp. (including S. equi). In vivo studies have also demonstrated the susceptibility of many strains of the following Gram-negative bacteria: E. coli and Proteus mirabilis. Because it does not resist destruction by penicillinase, it is not effective against penicillinase-producing bacteria, particularly resistant staphylococci. Most strains of Pseudomonas, Klebsiella and Aerobacter are resistant.

Ampicillin sodium diffuses readily into all body tissues and fluids, with the exception of brain and spinal fluid except when the meninges are inflamed. It produces high and persistent blood levels. Most of the ampicillin is excreted unchanged in the urine.

INDICATIONS

Ampicillin sodium is indicated in the treatment of susceptible strains of the organisms causing the following infections in the horse: Respiratory tract infections (pneumonia and strangles) due to Staphylococcus spp., Streptococcus spp. (including S. equi), E. coli, and Proteus mirabilis.

Skin and soft tissue infections (abscesses and wounds) due to Staphylococcus spp., Streptococcus spp., E. coli, and Proteus mirabilis.

As with all antibiotics, appropriate in vitroculturing and susceptibility testing of samples taken before treatment should be conducted.

CONTRAINDICATIONS

The use of this drug is contraindicated in animals with a history of an allergic reaction to penicillin.

ADVERSE REACTIONS

Ampicillin is a semisynthetic penicillin and has the potential for producing allergic reactions. If an allergic reaction occurs, administer epinephrine and/or steroids. Possible minor irritation at the injection site may occur.

WARNINGS

Restricted Drug (California) - Use only as Directed.

Do not use in horses intended for human consumption.

Not for human use.

CAUTION

Federal law restricts this drug to use by or on the order of a licensed veterinarian.

DOSAGE AND ADMINISTRATION

HORSES - The recommended dose is 3 mg per pound of body weight administered twice a day. Ampicillin sodium may be administered by either the intravenous or intramuscular route. Treatment should be continued 48 hours after all symptoms have subsided. If no response is seen in 4-5 days, diagnosis should be re-evaluated.

DIRECTIONS FOR USE

The dry filled vials should be reconstituted immediately before use by the addition of the appropriate amount of Sterile Water for Injection, USP indicated below. This results in a final concentration of approximately 300 mg per mL.

Vial Size | Amount of Diluent to be Added
1 Gram | 2.6 mL
3 Gram | 7.6 mL

Stability studies with the concentrated product (300 mg/mL) demonstrated that ampicillin is stable for 1 hour at room temperature (70°F - 75°F).

HOW SUPPLIED

Ampicillin Sodium is supplied in vials containing 1 gram and 3 grams of ampicillin activity.
Store dry powder at room temperature, 15°C to 30°C (59°F to 86°F).

NDC 86108-335-01 1 gm vial
NDC 86108-335-03 3 gm vial

Approved by FDA under ANADA # 200-335

Manufactured for:
US VET Inc.
Liverpool, NY 13088

INS16425 01 Rev. 02/2024

PACKAGE/LABEL PRINCIPAL DISPLAY PANEL

NDC 86108-335-01

AMPICILLIN SODIUM

For Intravenous or Intramuscular Use in Horses Only

1 GRAM

Each vial contains: Ampicillin sodium equivalent to 1 gram ampicillin.

CAUTION: Federal law restricts this drug to use by or on the order of a licensed veterinarian.

Mfd. For: US VET Inc. Liverpool, NY 13088